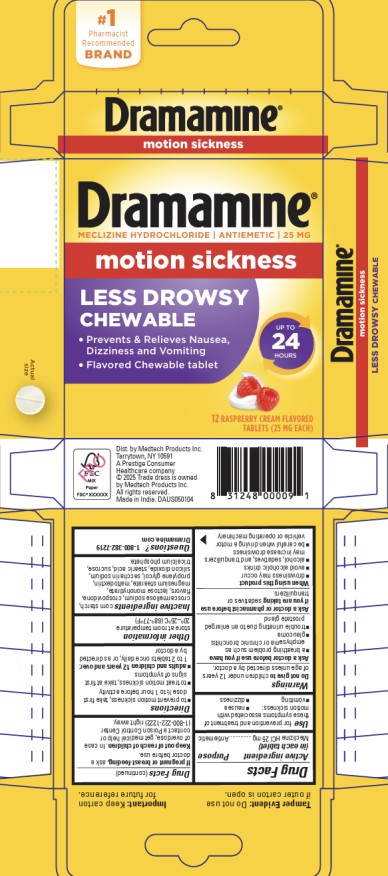 DRUG LABEL: DRAMAMINE
NDC: 63029-913 | Form: TABLET, CHEWABLE
Manufacturer: Medtech Products Inc.
Category: otc | Type: HUMAN OTC DRUG LABEL
Date: 20251223

ACTIVE INGREDIENTS: MECLIZINE HYDROCHLORIDE 25 mg/1 1
INACTIVE INGREDIENTS: STARCH, CORN; CROSCARMELLOSE SODIUM; CROSPOVIDONE; LACTOSE MONOHYDRATE; MAGNESIUM STEARATE; MALTODEXTRIN; PROPYLENE GLYCOL; SACCHARIN SODIUM; SILICON DIOXIDE; STEARIC ACID; SUCROSE; TRICALCIUM PHOSPHATE

Dramamine All Day LD Chewable Tablets Raspberry - 63029-913

Drug Facts

Active ingredient (in each tablet)

Meclizine HCl 25 mg

Purpose

Antiemetic

Use

for prevention and treatment of these symptoms associated with motion sickness:

■nausea ■vomiting ■dizziness

Warnings

Do not give to

children under 12 years of age unless directed by a doctor

Ask a doctor before use if you have

■a breathing problem such as emphysema or chronic bronchitis

■glaucoma

■trouble urinating due to an enlarged prostate gland

Ask a doctor or pharmacist before use if you are taking

sedatives or tranquilizers

When using this product

■drowsiness may occur

■avoid alcoholic drinks

■alcohol, sedatives, and tranquilizers may increase drowsiness

■be careful when driving a motor vehicle or operating machinery

If pregnant or breast-feeding,

ask a doctor before use.

Keep out of reach of children.

In case of overdose, get medical help or contact a Poison Control Center (1-800-222-1222) right away.

Directions

■to prevent motion sickness, take first dose ½ to 1 hour before activity

■to treat motion sickness, take at first signs of symptoms

■adults and children 12 years and over: 1 to 2 tablets once daily, or as directed by a doctor

Other information

■store at room temperature 20°–25°C (68°-77°F)

Inactive ingredients

corn starch, croscarmellose sodium, crospovidone, flavors, lactose monohydrate, magnesium stearate, maltodextrin, propylene glycol, saccharin sodium, silicon dioxide, stearic acid, sucrose, tricalcium phosphate.

Questions?

1-800-382-7219

Dramamine.com

PRINCIPAL DISPLAY PANEL

All Day Less Drowsy Chewable Formula

Dramamine®

Meclizine Hydrochloride | Antiemetic | 25 mg /Motion Sickness

12 Raspberry Cream Flavored Tablets (25 mg EACH)